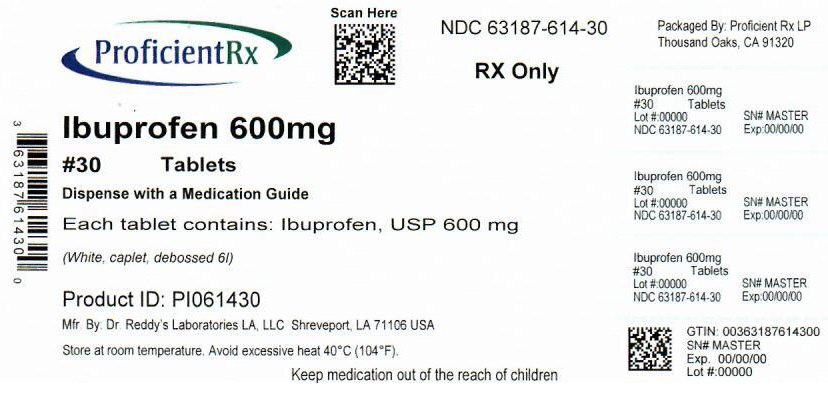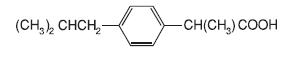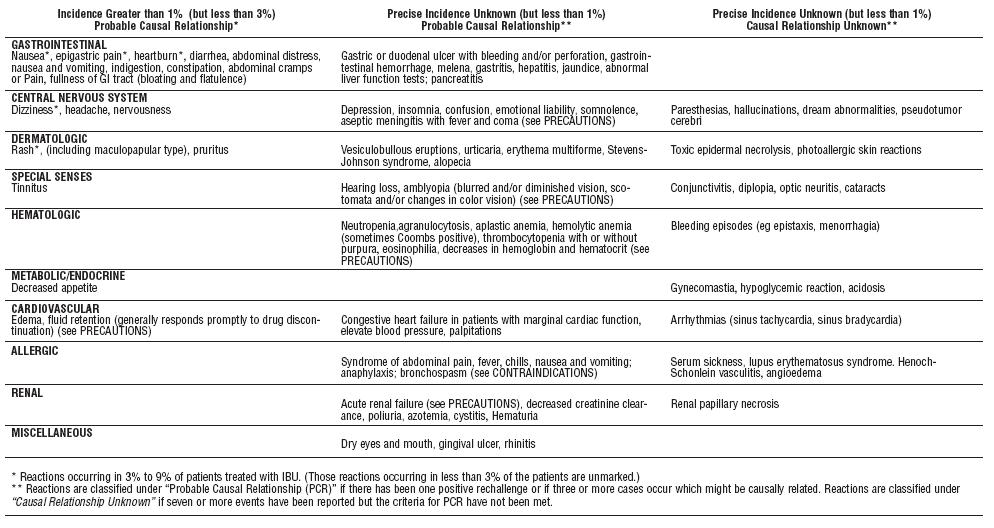 DRUG LABEL: IBU
NDC: 63187-614 | Form: TABLET
Manufacturer: Proficient Rx LP
Category: prescription | Type: HUMAN PRESCRIPTION DRUG LABEL
Date: 20251201

ACTIVE INGREDIENTS: Ibuprofen 600 mg/1 1
INACTIVE INGREDIENTS: carnauba wax; silicon dioxide; croscarmellose sodium; HYPROMELLOSE, UNSPECIFIED; magnesium stearate; MICROCRYSTALLINE CELLULOSE; polydextrose; POLYETHYLENE GLYCOL, UNSPECIFIED; polysorbate 80; titanium dioxide

IBU™ Tablets

BOXED WARNING

Cardiovascular Risk

1. NSAIDs may cause an increased risk of serious cardiovascularthrombotic events, myocardial infarction, and stroke,which can be fatal. This risk may increase with duration ofuse. Patients with cardiovascular disease or risk factors forcardiovascular disease may be at greater risk (See WARNINGS).
2. IBU tablets are contraindicated for treatment of peri-operativepain in the setting of coronary artery bypass graft (CABG)surgery (See WARNINGS).

Gastrointestinal Risk

1. NSAIDS cause an increased risk of serious gastrointestinaladverse events including bleeding, ulceration, and perforationof the stomach or intestines, which can be fatal. These eventscan occur at any time during use and without warning symptoms.Elderly patients are at greater risk for serious gastrointestinalevents. (See WARNINGS).

DESCRIPTION

IBU tablets contain the active ingredient ibuprofen, which is (±) -2 - (p - isobutylphenyl) propionic acid. Ibuprofen is a white powde rwith a melting point of 74-77° C and is very slightly soluble in water(<1 mg/mL) and readily soluble in organic solvents such as ethanol and acetone. The structural formula is represented below:

IBU, a nonsteroidal anti-inflammatory drug (NSAID), is availablein 400 mg, 600 mg, and 800 mg tablets for oral administration.Inactive ingredients: carnauba wax, colloidal silicon dioxide,croscarmellose sodium, hypromellose, magnesium stearate, microcrystallinecellulose, polydextrose, polyethylene glycol, polysorbate,titanium dioxide.

CLINICAL PHARMACOLOGY

IBU tablets contain ibuprofen which possesses analgesic andantipyretic activities. Its mode of action, like that of other NSAIDs, isnot completely understood, but may be related to prostaglandin synthetaseinhibition.

In clinical studies in patients with rheumatoid arthritis andosteoarthritis, Ibuprofen tablets have been shown to be comparableto aspirin in controlling pain and inflammation and to be associatedwith a statistically significant reduction in the milder gastrointestinalside effects (see ADVERSE REACTIONS). Ibuprofen may be well tolerated in some patients who have had gastrointestinal side effects with aspirin, but these patients when treated with IBU tablets should be carefully followed for signs and symptoms of gastrointestinal ulceration and bleeding. Although it is not definitely known whether ibuprofen causes less peptic ulceration than aspirin, in one study involving 885 patients with rheumatoid arthritis treated for up to one year, there were no reports of gastric ulceration with ibuprofen whereas frank ulceration was reported in 13 patients in the aspirin group (statistically significant p<.001).

Gastroscopic studies at varying doses show an increased tendency toward gastric irritation at higher doses. However, at comparable doses, gastric irritation is approximately half that seen with aspirin. Studies using 51Cr-tagged red cells indicate that fecal blood loss associated with Ibuprofen tablets in doses up to 2400 mg daily did not exceed the normal range, and was significantly less than that seen in aspirin-treated patients.

In clinical studies in patients with rheumatoid arthritis, Ibuprofen has been shown to be comparable to indomethacin in controlling the signs and symptoms of disease activity and to be associated with a statistically significant reduction of the milder gastrointestinal (see ADVERSE REACTIONS) and CNS side effects.

Ibuprofen may be used in combination with gold salts and/or corticosteroids.

Controlled studies have demonstrated that Ibuprofen is a more effective analgesic than propoxyphene for the relief of episiotomy pain, pain following dental extraction procedures, and for the relief of the symptoms of primary dysmenorrhea.

In patients with primary dysmenorrhea, Ibuprofen has been shown to reduce elevated levels of prostaglandin activity in the menstrual fluid and to reduce resting and active intrauterine pressure, as well as the frequency of uterine contractions. The probable mechanism ofaction is to inhibit prostaglandin synthesis rather than simply to provide analgesia.

The ibuprofen in IBU tablets is rapidly absorbed. Peak serum ibuprofen levels are generally attained one to two hours after administration. With single doses up to 800 mg, a linear relationship exists between amount of drug administered and the integrated area under the serum drug concentration vs time curve. Above 800 mg, however, the area under the curve increases less than proportional to increases in dose. There is no evidence of drug accumulation or enzyme induction.

The administration of Ibuprofen tablets either under fasting conditions or immediately before meals yields quite similar serum ibuprofen concentration-time profiles. When Ibuprofen is administered immediately after a meal, there is a reduction in the rate of absorption but no appreciable decrease in the extent of absorption. The bioavailability of the drug is minimally altered by the presence of food.

A bioavailability study has shown that there was no interference with the absorption of ibuprofen when given in conjunction with anantacid containing both aluminum hydroxide and magnesium hydroxide.

Ibuprofen is rapidly metabolized and eliminated in the urine. The excretion of ibuprofen is virtually complete 24 hours after the last dose. The serum half-life is 1.8 to 2.0 hours.

Studies have shown that following ingestion of the drug, 45% to79% of the dose was recovered in the urine within 24 hours as metabolite A (25%), (+)-2-[p-(2hydroxymethyl-propyl) phenyl] propionic acid and metabolite B (37%), (+)-2-[p-(2carboxypropyl)phenyl]propionic acid; the percentages of free and conjugated ibuprofen were approximately 1% and 14%, respectively.

INDICATIONS AND USAGE

Carefully consider the potential benefits and risks of Ibuprofentablets and other treatment options before deciding to use Ibuprofen.Use the lowest effective dose for the shortest duration consistent withindividual patient treatment goals (see WARNINGS).

IBU tablets are indicated for relief of the signs and symptoms of rheumatoid arthritis and osteoarthritis.

IBU tablets are indicated for relief of mild to moderate pain.

IBU tablets are also indicated for the treatment of primary dysmenorrhea.

Controlled clinical trials to establish the safety and effectiveness of IBU tablets in children have not been conducted.

CONTRAINDICATIONS

IBU tablets are contraindicated in patients with known hypersensitivityto ibuprofen.

IBU tablets should not be given to patients who have experienced asthma, urticaria, or allergic-type reactions after taking aspirin orother NSAIDs. Severe, rarely fatal, anaphylactic-like reactions to NSAIDs have been reported in such patients (see WARNINGS, Anaphylactoid Reactions, and PRECAUTIONS, Preexisting Asthma).

IBU tablets are contraindicated for the treatment of peri-operative pain in the setting of coronary artery bypass graft (CABG) surgery(see WARNINGS).

WARNINGS

CARDIOVASCULAR EFFECTS

Cardiovascular Thrombotic Events

Clinical trials of several COX-2 selective and nonselective NSAIDsof up to three years duration have shown an increased risk of seriouscardiovascular (CV) thrombotic events, myocardial infarction, andstroke, which can be fatal. All NSAIDs, both COX-2 selective and nonselective,may have a similar risk. Patients with known CV disease orrisk factors for CV disease may be at greater risk. To minimize thepotential risk for an adverse CV event in patients treated with anNSAID, the lowest effective dose should be used for the shortestduration possible. Physicians and patients should remain alert for thedevelopment of such events, even in the absence of previous CVsymptoms. Patients should be informed about the signs and/orsymptoms of serious CV events and the steps to take if they occur.

There is no consistent evidence that concurrent use of aspirin mitigatesthe increased risk of serious CV thrombotic events associatedwith NSAID use. The concurrent use of aspirin and an NSAID doesincrease the risk of serious GI events (see GI WARNINGS).

Two large, controlled clinical trials of a COX-2 selective NSAID forthe treatment of pain in the first 10-14 days following CABG surgeryfound an increased incidence of myocardial infarction and stroke (see CONTRAINDICATIONS).

Hypertension

NSAIDs including IBU tablets, can lead to onset of new hypertensionor worsening of preexisting hypertension, either of which maycontribute to the increased incidence of CV events. Patients takingthiazides or loop diuretics may have impaired response to these therapieswhen taking NSAIDs. NSAIDs, including IBU tablets, should beused with caution in patients with hypertension. Blood pressure (BP)should be monitored closely during the initiation of NSAID treatmentand throughout the course of therapy.

Congestive Heart Failure and Edema

Fluid retention and edema have been observed in some patients taking NSAIDs. IBU tablets should be used with caution in patients with fluid retention or heart failure.

Gastrointestinal Effects - Risk of Ulceration, Bleeding, and Perforation

NSAIDs, including IBU tablets, can cause serious gastrointestinal(GI) adverse events including inflammation, bleeding, ulceration, and perforation of the stomach, small intestine, or large intestine, which can be fatal. These serious adverse events can occur at any time, with or without warning symptoms, in patients treated with NSAIDs. Only one in five patients, who develop a serious upper GI adverse event on NSAID therapy, is symptomatic. Upper GI ulcers, gross bleeding, or perforation caused by NSAIDs occur in approximately 1% of patientstreated for 3-6 months, and in about 2-4% of patients treated for oneyear. These trends continue with longer duration of use, increasing the likelihood of developing a serious GI event at some time during the course of therapy. However, even short-term therapy is not without risk. NSAIDs should be prescribed with extreme caution in thosewith a prior history of ulcer disease or gastrointestinal bleeding.Patients with a prior history of peptic ulcer disease and/or gastrointestinal bleeding who use NSAIDs have a greater than 10-fold increased risk for developing a GI bleed compared to patients treatedwith neither of these risk factors. Other factors that increase the riskof GI bleeding in patients treated with NSAIDs include concomitant use of oral corticosteroids or anticoagulants, longer duration of NSAID therapy, smoking, use of alcohol, older age, and poor general health status. Most spontaneous reports of fatal GI events are in elderly or debilitated patients and therefore, special care should be taken in treating this population. To minimize the potential risk for an adverse GI event in patients treated with an NSAID, the lowest effective dose should be used for the shortest possible duration. Patients and physicians should remain alert for signs and symptoms of GIulcerations and bleeding during NSAID therapy and promptly initiate additional evaluation and treatment if a serious GI event is suspected.This should include discontinuation of the NSAID until a serious GI adverse event is ruled out. For high-risk patients, alternate therapies that do not involve NSAIDs should be considered.

Renal Effects

Long-term administration of NSAIDs has resulted in renal papillary necrosis and other renal injury. Renal toxicity has also been seen in patients in whom renal prostaglandins have a compensatory role in the maintenance of renal perfusion. In these patients, administration of a NSAID may cause a dose dependent reduction in prostaglandin formation and, secondarily, in renal blood flow, which may precipitate overt renal decompensation. Patients at greatest riskof this reaction are those with impaired renal function, heart failure,liver dysfunction, those taking diuretics and ACE inhibitors, and the elderly. Discontinuation of NSAID therapy is usually followed by recovery to the pretreatment state.

Advanced Renal Disease

No information is available from controlled clinical studies regarding the use of Ibuprofen tablets in patients with advanced renal disease.Therefore, treatment with IBU tablets is not recommended in these patients with advanced renal disease. If IBU tablet therapy must be initiated, close monitoring of the patients renal function is advisable.

Anaphylactoid Reactions

As with other NSAIDs, anaphylactoid reactions may occur inpatients without known prior exposure to IBU tablets. IBU tablets should not be given to patients with the aspirin triad. This symptom complex typically occurs in asthmatic patients who experience rhinitis with or without nasal polyps, or who exhibit severe, potentially fatal bronchospasm after taking aspirin or other NSAIDs (see CONTRAINDICATIONS and PRECAUTIONS, Preexisting Asthma).Emergency help should be sought in cases where an anaphylactoidreaction occurs.

Skin Reactions

NSAIDs, including IBU tablets, can cause serious skin adverse events such as exfoliative dermatitis, Stevens-Johnson Syndrome(SJS), and toxic epidermal necrolysis (TEN), which can be fatal.These serious events may occur without warning. Patients should be informed about the signs and symptoms of serious skin manifestations and use of the drug should be discontinued at the first appearance of skin rash or any other sign of hypersensitivity.

Pregnancy

In late pregnancy, as with other NSAIDs, IBU tablets should beavoided because it may cause premature closure of the ductus arteriosus.

PRECAUTIONS

General

IBU tablets cannot be expected to substitute for corticosteroids orto treat corticosteroid insufficiency. Abrupt discontinuation of corticosteroidsmay lead to disease exacerbation. Patients on prolongedcorticosteroid therapy should have their therapy tapered slowly if adecision is made to discontinue corticosteroids.

The pharmacological activity of IBU tablets in reducing fever andinflammation may diminish the utility of these diagnostic signs indetecting complications of presumed noninfectious, painful conditions.

Hepatic effects

Borderline elevations of one or more liver tests may occur in upto 15% of patients taking NSAIDs, including IBU tablets. These laboratoryabnormalities may progress, may remain unchanged, or maybe transient with continuing therapy. Notable elevations of ALT orAST (approximately three or more times the upper limit of normal)have been reported in approximately 1% of patients in clinical trialswith NSAIDs. In addition, rare cases of severe hepatic reactions,including jaundice, fulminant hepatitis, liver necrosis, and hepaticfailure, some of them with fatal outcomes have been reported. Apatient with symptoms and/or signs suggesting liver dysfunction, orwith abnormal liver test values, should be evaluated for evidence ofthe development of a more severe hepatic reaction while on therapywith IBU tablets. If clinical signs and symptoms consistent with liverdisease develop, or if systemic manifestations occur (e.g.,eosinophilia, rash, etc.), IBU tablets should be discontinued.

Hematological effects

Anemia is sometimes seen in patients receiving NSAIDs, includingIBU tablets. This may be due to fluid retention, occult or gross GIblood loss, or an incompletely described effect upon erythropoiesis.Patients on long-term treatment with NSAIDs, including IBU tablets,should have their hemoglobin or hematocrit checked if they exhibitany signs or symptoms of anemia.

In two postmarketing clinical studies the incidence of a decreasedhemoglobin level was greater than previously reported. Decrease inhemoglobin of 1 gram or more was observed in 17.1% of 193patients on 1600 mg ibuprofen daily (osteoarthritis), and in 22.8% of189 patients taking 2400 mg of ibuprofen daily (rheumatoid arthritis).Positive stool occult blood tests and elevated serum creatinine levelswere also observed in these studies.

NSAIDs inhibit platelet aggregation and have been shown to prolongbleeding time in some patients. Unlike aspirin, their effect onplatelet function is quantitatively less, of shorter duration, and reversible.

Patients receiving IBU tablets who may be adversely affected byalterations in platelet function, such as those with coagulation disordersor patients receiving anticoagulants should be carefully monitored.

Preexisting asthma

Patients with asthma may have aspirin-sensitive asthma. The useof aspirin in patients with aspirin-sensitive asthma has been associatedwith severe bronchospasm, which can be fatal. Since cross reactivity,including bronchospasm, between aspirin and NSAIDs hasbeen reported in such aspirin-sensitive patients, IBU tablets shouldnot be administered to patients with this form of aspirin sensitivityand should be used with caution in patients with preexisting asthma.

Ophthalmological effects.

Blurred and/or diminished vision, scotomata, and/or changes incolor vision have been reported. If a patient develops such complaintswhile receiving IBU tablets, the drug should be discontinued, and thepatient should have an ophthalmologic examination which includescentral visual fields and color vision testing.

Aseptic Meningitis

Aseptic meningitis with fever and coma has been observed on rareoccasions in patients on ibuprofen therapy. Although it is probablymore likely to occur in patients with systemic lupus erythematosusand related connective tissue diseases, it has been reported inpatients who do not have an underlying chronic disease. If signs orsymptoms of meningitis develop in a patient on IBU tablets, the possibilityof its being related to IBU tablets should be considered.

Information for Patients

Patients should be informed of the following information beforeinitiating therapy with an NSAID and periodically during the course ofongoing therapy. Patients should also be encouraged to read theNSAID Medication Guide that accompanies each prescription dispensed

• IBU tablets like other NSAIDs, may cause serious CV side effects,such as MI or stroke, which may result in hospitalization and evendeath. Although serious CV events can occur without warningsymptoms, patients should be alert for the signs and symptoms ofchest pain, shortness of breath, weakness, slurring of speech, andshould ask for medical advice when observing any indicative sign orsymptoms. Patients should be apprised of the importance of thisfollow-up (see WARNINGS, Cardiovascular Effects).

• IBU tablets, like other NSAIDs, can cause GI discomfort and, rarely,serious GI side effects, such as ulcers and bleeding, which mayresult in hospitalization and even death. Although serious GI tractulcerations and bleeding can occur without warning symptoms,patients should be alert for the signs and symptoms of ulcerationsand bleeding, and should ask for medical advice when observingany indicative signs or symptoms including epigastric pain, dyspepsia,melena, and hematemesis. Patients should be apprised of theimportance of this follow-up (see WARNINGS, Gastrointestinal Effects-Risk of Ulceration, Bleeding and Perforation).

• IBU tablets, like other NSAIDs, can cause serious skin side effectssuch as exfoliative dermatitis, SJS and TEN, which may result inhospitalization and even death. Although serious skin reactions mayoccur without warning, patients should be alert for the signs andsymptoms of skin rash and blisters, fever, or other signs of hypersensitivitysuch as itching, and should ask for medical advice whenobserving any indicative sign or symptoms. Patients should beadvised to stop the drug immediately if they develop any type ofrash and contact their physicians as soon as possible.

• Patients should promptly report signs or symptoms of unexplainedweight gain or edema to their physicians.

• Patients should be informed of the warning signs and symptoms ofhepatotoxicity (e.g., nausea, fatigue, lethargy, pruritus, jaundice,right upper quadrant tenderness and “flu-like” symptoms). If theseoccur, patients should be instructed to stop therapy and seek immediatemedical therapy.

• Patients should be informed of the signs of an anaphylactoid reaction(e.g. difficulty breathing, swelling of the face or throat). If theseoccur, patients should be instructed to seek immediate emergencyhelp (see WARNINGS).

• In late pregnancy, as with other NSAIDs, IBU tablets should beavoided because it may cause premature closure of the ductus arteriosus.

Laboratory Tests

Because serious GI tract ulcerations and bleeding can occur withoutwarning symptoms, physicians should monitor for signs orsymptoms of GI bleeding. Patients on long-term treatment withNSAIDs should have their CBC and chemistry profile checked periodically.If clinical signs and symptoms consistent with liver or renaldisease develop, systemic manifestations occur (e.g., eosinophilia,rash etc.), or abnormal liver tests persist or worsen, IBU tabletsshould be discontinued.

Drug Interactions

ACE-inhibitors:Reports suggest that NSAIDs may diminish the antihypertensiveeffect of ACE-inhibitors. This interaction should be given considerationin patients taking NSAIDs concomitantly with ACE-inhibitors.

AspirinWhen IBU tablets are administered with aspirin, its protein bindingis reduced, although the clearance of free IBU tablets is notaltered. The clinical significance of this interaction is not known; however,as with other NSAIDs, concomitant administration of ibuprofenand aspirin is not generally recommended because of the potential forincreased adverse effects.

Diuretics

Clinical studies, as well as post marketing observations, haveshown that Ibuprofen tablets can reduce the natriuretic effect-offurosemide and thiazides in some patients. This response has beenattributed to inhibition of renal prostaglandin synthesis. During concomitanttherapy with NSAIDs, the patient should be observed closelyfor signs of renal failure (see PRECAUTIONS, Renal Effects), aswell as to assure diuretic efficacy.

Lithium

Ibuprofen produced an elevation of plasma lithium levels and areduction in renal lithium clearance in a study of eleven normal volunteers.The mean minimum lithium concentration increased 15%and the renal clearance of lithium was decreased by 19% during thisperiod of concomitant drug administration.This effect has been attributed to inhibition of renal prostaglandinsynthesis by ibuprofen. Thus, when ibuprofen and lithium are administeredconcurrently, subjects should be observed carefully for signsof lithium toxicity. (Read circulars for lithium preparation before useof such concurrent therapy.)

Methotrexate

NSAIDs have been reported to competitively inhibit methotrexateaccumulation in rabbit kidney slices. This may indicate that they couldenhance the toxicity of methotrexate. Caution should be used whenNSAIDs are administered concomitantly with methotrexate.

Warfarin-type anticoagulants

Several short-term controlled studies failed to show that Ibuprofentablets significantly affected prothrombin times or a variety of otherclotting factors when administered to individuals on coumarin-typeanticoagulants. However, because bleeding has been reported whenIBU tablets and other NSAIDs have been administered to patients oncoumarin-type anticoagulants, the physician should be cautiouswhen administering IBU tablets to patients on anticoagulants. Theeffects of warfarin and NSAIDs on GI bleeding are synergistic, suchthat the users of both drugs together have a risk of serious GI bleedinghigher than users of either drug alone.

H-2 Antagonists

In studies with human volunteers, co-administration of cimetidineor ranitidine with ibuprofen had no substantive effect on ibuprofenserum concentrations.

Pregnancy

Teratogenic effects: Pregnancy Category C

Reproductive studies conducted in rats and rabbits have notdemonstrated evidence of developmental abnormalities. However,animal reproduction studies are not always predictive of humanresponse. There are no adequate and well-controlled studies in pregnantwomen. Ibuprofen should be used in pregnancy only if thepotential benefit justifies the potential risk to the fetus.

Nonteratogenic effects

Because of the known effects of NSAIDs on the fetal cardiovascularsystem (closure of ductus arteriosus), use during late pregnancyshould be avoided.

Labor and Delivery

In rat studies with NSAIDs, as with other drugs known to inhibitprostaglandin synthesis, an increased incidence of dystocia, delayedparturition, and decreased pup survival occurred. The effects of IBUtablets on labor and delivery in pregnant women are unknown.

Nursing Mothers

It is not known whether this drug is excreted in human milk.Because many drugs are excreted in human-milk and because of thepotential for serious adverse reactions in nursing infants from IBUtablets, a decision should be made whether to discontinue nursing ordiscontinue the drug, taking into account the importance of the drugto the mother.

Pediatric Use

Safety and effectiveness of IBU tablets in pediatric patients havenot been established.

Geriatric Use

As with any NSAIDs, caution should be exercised in treating theelderly (65 years and older).

ADVERSE REACTIONS

The most frequent type of adverse reaction occurring withIbuprofen tablets is gastrointestinal. In controlled clinical trials thepercentage of patients reporting one or more gastrointestinal complaintsranged from 4% to 16%.

In controlled studies when Ibuprofen tablets were compared toaspirin and indomethacin in equally effective doses, the overall incidenceof gastrointestinal complaints was about half that seen in eitherthe aspirin- or indomethacin-treated patients.

Adverse reactions observed during controlled clinical trials at anincidence greater than 1% are listed in the table. Those reactions listedin Column one encompass observations in approximately 3,000patients. More than 500 of these patients were treated for periods ofat least 54 weeks.

Still other reactions occurring less frequently than 1 in 100 werereported in controlled clinical trials and from marketing experience.These reactions have been divided into two categories: Column twoof the table lists reactions with therapy with Ibuprofen tablets wherethe probability of a causal relationship exists: for the reactions inColumn three, a causal relationship with Ibuprofen tablets has notbeen established.

Reported side effects were higher at doses of 3200 mg/day thanat doses of 2400 mg or less per day in clinical trials of patients withrheumatoid arthritis. The increases in incidence were slight and stillwithin the ranges reported in the table.

OVERDOSAGE

Approximately 11⁄2 hours after the reported ingestion of from 7 to10 Ibuprofen tablets (400 mg), a 19-month old child weighing 12 kgwas seen in the hospital emergency room, apneic and cyanotic,responding only to painful stimuli. This type of stimulus, however,was sufficient to induce respiration. Oxygen and parenteral fluidswere given; a greenish-yellow fluid was aspirated from the stomachwith no evidence to indicate the presence of ibuprofen. Two hoursafter ingestion the child’s condition seemed stable; she still respondedonly to painful stimuli and continued to have periods of apnea lastingfrom 5 to 10 seconds. She was admitted to intensive care andsodium bicarbonate was administered as well as infusions of dextroseand normal saline. By four hours post-ingestion she could bearoused easily, sit by herself and respond to spoken commands.Blood level of ibuprofen was 102.9 μg/mL approximately 81⁄2 hoursafter accidental ingestion. At 12 hours she appeared to be completelyrecovered.

In two other reported cases where children (each weighingapproximately 10 kg) accidentally, acutely ingested approximately120 mg/kg, there were no signs of acute intoxication or late sequelae.Blood level in one child 90 minutes after ingestion was 700 μg/mL —about 10 times the peak levels seen in absorption-excretion studies.A 19-year old male who had taken 8,000 mg of ibuprofen over aperiod of a few hours complained of dizziness, and nystagmus wasnoted. After hospitalization, parenteral hydration and three days bedrest, he recovered with no reported sequelae.

In cases of acute overdosage, the stomach should be emptied byvomiting or lavage, though little drug will likely be recovered if morethan an hour has elapsed since ingestion. Because the drug is acidicand is excreted in the urine, it is theoretically beneficial to administeralkali and induce diuresis. In addition to supportive measures, the useof oral activated charcoal may help to reduce the absorption andreabsorption of Ibuprofen tablets.

DOSAGE AND ADMINISTRATION

Carefully consider the potential benefits and risks of IBU tabletsand other treatment options before deciding to use IBU tablets. Usethe lowest effective dose for the shortest duration consistent withindividual patient treatment goals (see WARNINGS).

After observing the response to initial therapy with IBU tablets, thedose and frequency should be adjusted to suit an individual patient’sneeds.Do not exceed 3200 mg total daily dose. If gastrointestinal complaintsoccur, administer IBU tablets with meals or milk.

Rheumatoid arthritis and osteoarthritis, including flare-ups ofchronic disease:

Suggested Dosage: 1200 mg-3200 mg daily (400 mg, 600 mg or800 mg tid or qid). Individual patients may show a better responseto 3200 mg daily, as compared with 2400 mg, although in well-controlledclinical trials patients on 3200 mg did not show a better meanresponse in terms of efficacy. Therefore, when treating patients with3200 mg/day, the physician should observe sufficient increased clinicalbenefits to offset potential increased risk.The dose should be tailored to each patient, and may be loweredor raised depending on the severity of symptoms either at time of initiatingdrug therapy or as the patient responds or fails to respond.In general, patients with rheumatoid arthritis seem to require higherdoses of IBU tablets than do patients with osteoarthritis.

The smallest dose of IBU tablets that yields acceptable controlshould be employed. A linear blood level dose-response relationshipexists with single doses up to 800 mg (See CLINICAL PHARMACOLOGYfor effects of food on rate of absorption).

The availability of three tablet strengths facilitates dosage adjustment.In chronic conditions, a therapeutic response to therapy with IBU tablets is sometimes seen in a few days to a week but most often isobserved by two weeks. After a satisfactory response has beenachieved, the patient’s dose should be reviewed and adjusted asrequired.

Mild to moderate pain:

400 mg every 4 to 6 hours as necessaryfor relief of pain.In controlled analgesic clinical trials, doses of Ibuprofen tabletsgreater than 400 mg were no more effective than the 400 mg dose.

Dysmenorrhea:

For the treatment of dysmenorrhea, beginningwith the earliest onset of such pain, IBU tablets should be given in adose of 400 mg every 4 hours as necessary for the relief of pain.

HOW SUPPLIED

IBU tablets are available in the following strengths, colors and sizes:

600 mg (white, caplet, debossed 6I)

Bottles of 15 NDC 63187-614-15

Bottles of 20 NDC 63187-614-20

Bottles of 21 NDC 63187-614-21

Bottles of 28 NDC 63187-614-28

Bottles of 30 NDC 63187-614-30

Bottles of 40 NDC 63187-614-40

Bottles of 42 NDC 63187-614-42

Bottles of 45 NDC 63187-614-45

Bottles of 60 NDC 63187-614-60

Bottles of 90 NDC 63187-614-90

Store at room temperature. Avoid excessive heat 40°C (104°F).

Manufactured by:

Dr. Reddy’s Laboratories Louisiana, LLC

Shreveport, LA 71106 USA

Revised, October 2013

Repackaged by:

Proficient Rx LP

Thousand Oaks, CA 91320

MEDICATION GUIDE

Medication Guide for Non-Steroidal Anti-Inflammatory Drugs (NSAIDs)

(See the end of this Medication Guide for a list of prescription NSAID medicines.)

What it the most important information I should know about medicines called Non-Steroidal Anti-Inflammatory Drugs (NSAIDs)?

NSAID medicines may increase the chance of a heart attack or stroke that can lead to death.

This chance increases:

• with longer use of NSAID medicines • in people who have heart disease

NSAID medicines should never be used right before or after a heart surgery called a “coronary artery bypass graft (CABG).”

NSAID medicines can cause ulcers and bleeding in the stomach and intestines at any time during treatment. Ulcers and bleeding:

• can happen without warning symptoms • may cause death

The chance of a person getting an ulcer or bleeding increases with:

• taking medicines called “corticosteroids” • drinking alcohol and “anticoagulants”

• older age

• longer use • having poor health

• smoking

NSAID medicines should only be used:

• exactly as prescribed

• for the shortest time needed

• at the lowest dose possible for your treatment

What are Non-Steroidal Anti-Inflammatory Drugs (NSAIDs) ?

NSAID medicines are used to treat pain and redness, swelling, and heat (inflammation) from medical conditions such as:

• different types of arthritis

• menstrual cramps and other types of short-term pain

Who should not take a Non-Steroidal Anti-Inflammatory Drug (NSAID) ? Do not take an NSAID medicine:

• if you had an asthma attack, hives, or other allergic reaction with aspirin or any other NSAID medicine

• for pain right before or after heart bypass surgery

Tell your healthcare provider:

• about all of your medical conditions

• about all of the medicines you take. NSAIDs and some other medicines can interact with each other and cause serious side effects.

Keep a list of your medicines to show to your healthcare provider and pharmacist.

• if you are pregnant. NSAID medicines should not be used by pregnant women late in their pregnancy.

• if you are breastfeeding. Talk to your doctor.

What are the possible side effects of Non-Steroidal Anti-Inflammatory Drugs (NSAIDs)?

Serious side effect | Other side effect include
• heart attack | • stomach pain
• stroke | • constipation
• high blood pressure | • diarrhea
• heart failure from body swelling (fluid retention) | • gas
• kidney problems including kidney failure | • heartburn
• bleeding and ulcers in the stomach and intestine | • nausea
• low red blood cells (anemia) | • vomiting
• life-threatening skin reactions | • dizziness
• life-threatening allergic reactions
• liver problems including liver failure
• asthma attacks in people who have asthma

Get emergency help right away if you have any of the following symptoms:

• shortness of breath or trouble breathing • slurred speech

• chest pain • swelling of the face or throat

• weakness in one part or side of your body

Stop your NSAID medicine and call your healthcare provider right away if you have any of the following symptoms:

• nausea

• vomit blood

• more tired or weaker than usual

• there is blood in your bowel movement or sticky it is black and sticky like tar

• itching

• skin rash or blister with fever

• your skin or eyes look yellow

• unusual weight gain

• stomach pain

• swelling of the arms and legs, hands and feet

• flu-like symptoms

These are not all the side effects with NSAID medicines. Talk to your healthcare provider or pharmacist for more information about NSAID medicines.

Call your doctor for medical advice about side effects. You may report side effects to FDA at 1-800-FDA-1088.Other information about Non-Steroidal Anti-Inflammatory Drugs (NSAIDs)

•Aspirin is an NSAID medicine but it does not increase the chance of a heart attack. Aspirin can cause bleeding in the brain, stomach, and intestines. Aspirin can also cause ulcers in the stomach and intestines.

• Some of these NSAID medicines are sold in lower doses without a prescription (over-the-counter) Talk to your healthcare provider before using over- the-counter NSAIDs for more than 10 days.

NSAID medicines that need a prescription

Generic | Trade Name
Celecoxib | Celebrex
Diclofenac | Cataflam, Voltaren, Arthrotec (combined with misoprostol)
Diflunisal | Dolobid
Etodolac | Lodine, Lodine XL
Fenoprofen | Nalfon, Nalfon 200
Flurbiprofen | Ansaid
Ibuprofen | Motrin, Tab-Profen, Vicoprofen* (combined with hydrocodone), Combunox (combined with oxycodone)
Indomethacin | Indocin, Indocin SR, Indo-Lemmon, Indomethagan
Ketoprofen | Oruvail
Ketorolac | Toradol
Mefenamic Acid | Ponstel
Meloxicam | Mobic
Nabumetone | Relafen
Naproxen | Naprosyn, Anaprox, Anaprox DS, EC-Naprosyn, Naprelan, Naprapac (copackaged with lansoprazole)
Oxaprozin | Daypro
Piroxicam | Feldene
Sulindac | Clinoril
Tolmetin | Tolectin, Tolectin DS, Tolectin 600

*Vicoprofen contains the same dose of ibuprofen as over-the-counter (OTC) NSAIDS, and is usually used for less than 10 days to treat pain. The OTC NSAID label warns that long term continuous use may increase the risk of heart attack or stroke

PACKAGE LABEL.PRINCIPAL DISPLAY PANEL SECTION

PRINICPAL DISPLAY PANEL 600 mg -30 count